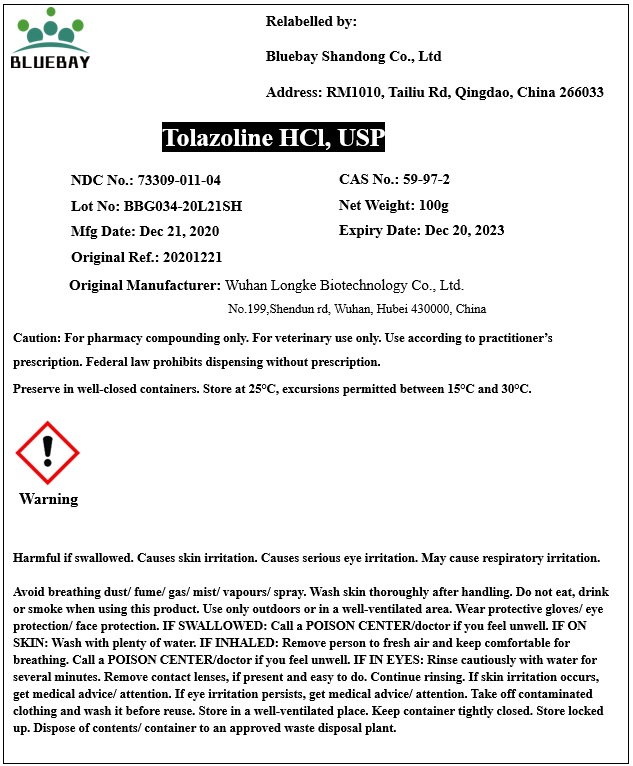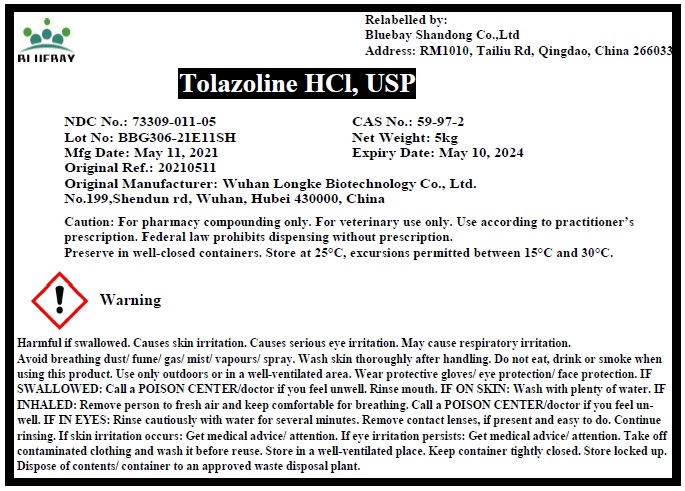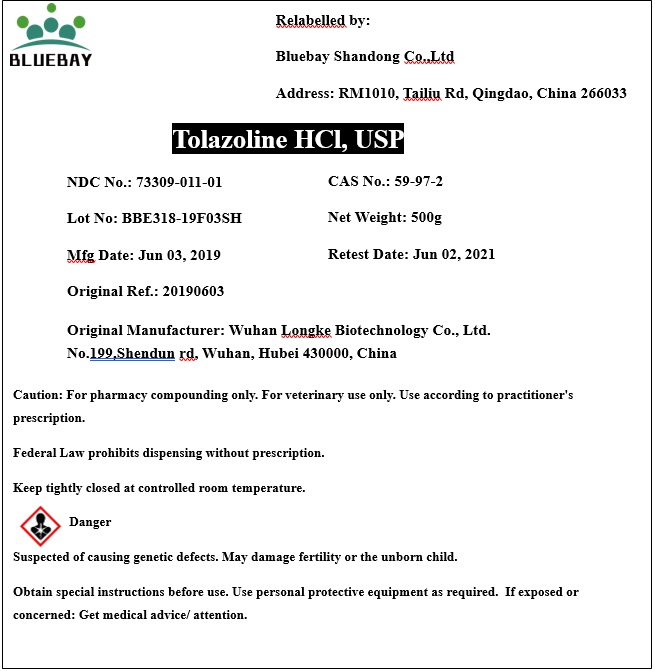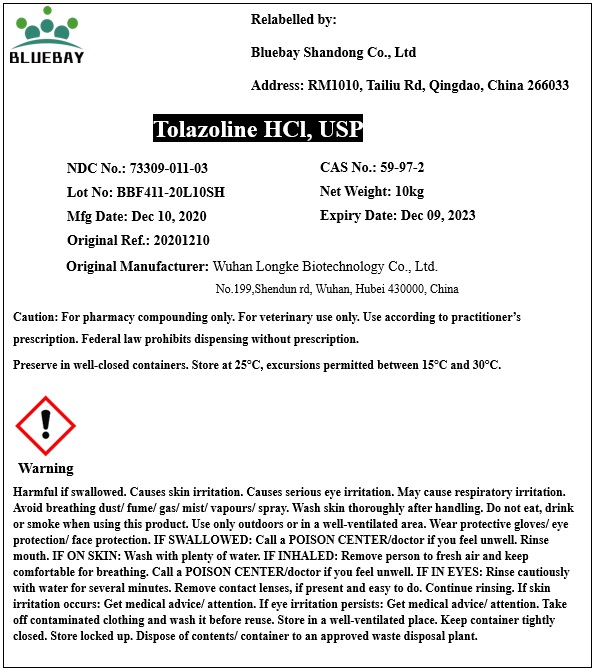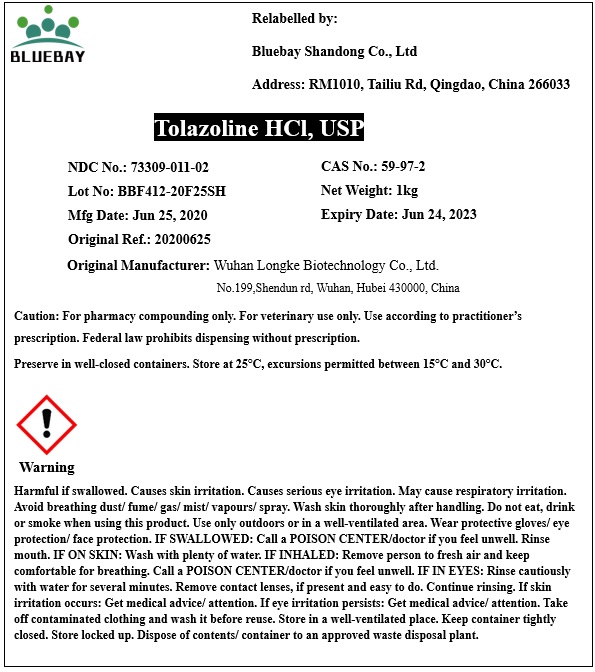 DRUG LABEL: Tolazoline HCl
NDC: 73309-011 | Form: POWDER
Manufacturer: BLUEBAY SHANDONG CO.,LTD
Category: other | Type: BULK INGREDIENT
Date: 20210615

ACTIVE INGREDIENTS: TOLAZOLINE HYDROCHLORIDE 1 g/1 g

Tolazoline HCl